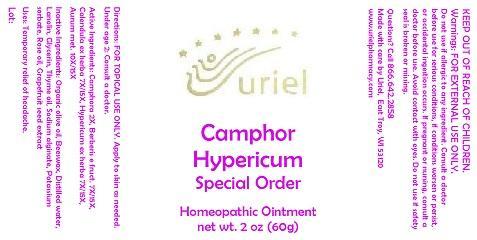 DRUG LABEL: Camphor Hypericum Special Order
NDC: 48951-3186 | Form: OINTMENT
Manufacturer: Uriel Pharmacy Inc.
Category: homeopathic | Type: HUMAN OTC DRUG LABEL
Date: 20141105

ACTIVE INGREDIENTS: CAMPHOR (NATURAL) 2 [hp_X]/1 g; BERBERIS VULGARIS ROOT BARK 7 [hp_X]/1 g; CALENDULA OFFICINALIS FLOWERING TOP 7 [hp_X]/1 g; ST. JOHN'S WORT 7 [hp_X]/1 g; GOLD 10 [hp_X]/1 g
INACTIVE INGREDIENTS: OLIVE OIL; YELLOW WAX; WATER; LANOLIN; GLYCERIN; THYME OIL; SODIUM ALGINATE; POTASSIUM SORBATE; ROSE OIL; CITRUS PARADISI SEED

Camphor Hypericum Special Order

INDICATIONS AND USAGE

Directions: FOR TOPICAL USE ONLY.

DOSAGE AND ADMINISTRATION

Apply to skin as needed. Under age 2: Consult a doctor.

ACTIVE INGREDIENT

Active Ingredients: Camphora 2X, Berberis e fruct. 7X/15X, Calendula ex herba 7X/15X, Hypericum ex herba 7X/15X, Aurum met. 10X/15X

INACTIVE INGREDIENT

Inactive Ingredients: Organic olive oil, Beeswax, Distilled water, Lanolin, Glycerin, Thyme oil, Sodium alginate, Potassium sorbate, Rose oil, Grapefruit seed extract

PURPOSE

Uses: Temporary relief of headache.

KEEP OUT OF REACH OF CHILDREN.

WARNINGS

Warnings: FOR EXTERNAL USE ONLY. Do not use if allergic to any ingredient. Consult a doctor before use for serious conditions, if conditions worsen or persist, or accidental ingestion occurs. If pregnant or nursing, consult a doctor before use. Avoid contact with eyes. Do not use if safety seal is broken or missing.

QUESTIONS

Questions? Call 866.642.2858 Made with care by Uriel, East Troy, WI 53120 www.urielpharmacy.com